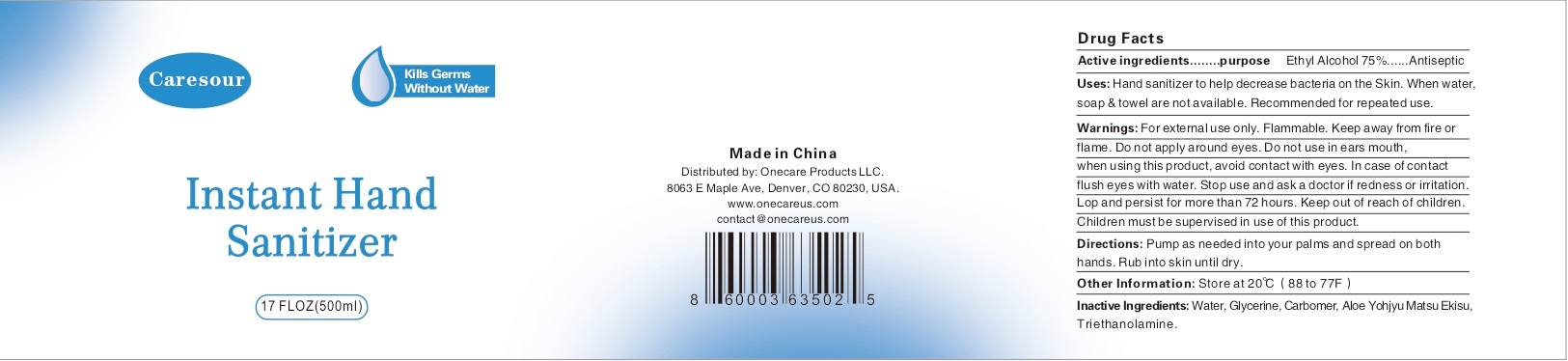 DRUG LABEL: Caresour Instant Hand Sanitizer
NDC: 74614-006 | Form: SOLUTION
Manufacturer: TAIZHOU BENGTE FURNITURE CO.,LTD
Category: otc | Type: HUMAN OTC DRUG LABEL
Date: 20200414

ACTIVE INGREDIENTS: ALCOHOL 75 mL/100 mL
INACTIVE INGREDIENTS: WATER; TROLAMINE; GLYCERIN; PROPYLENE GLYCOL; SODIUM HYDROXIDE

Active ingredient

Ethyl Alcohol 75%

Purpose

Antiseptic

Use

Hand sanitizer to help decrease bacteria on the skin. When water, soap and towel are not available. Recommended for repeated use.

KEEP OUT OF REACH OF CHILDREN

Children must be supervised in use of this product.

warnings:

Flamable, keep away from fire and flame.

For external use only

Do not apply around eyes. Do not use in ears, mouth.

When using this product, avoid contact with eyes. In case of contact, flush eyes with water.

Stop use and ask a doctor if redness or irritation develop and persist for more than 72 hours

DOSAGE AND ADMINISTRATION

Pump as needed into your palms and spread on both hands. Rub into skin until dry.

Inactive ingredients

Water, Glycerin, Carbomer, Aloe Yohjyu Matsu Ekisu, Triethanolamine.